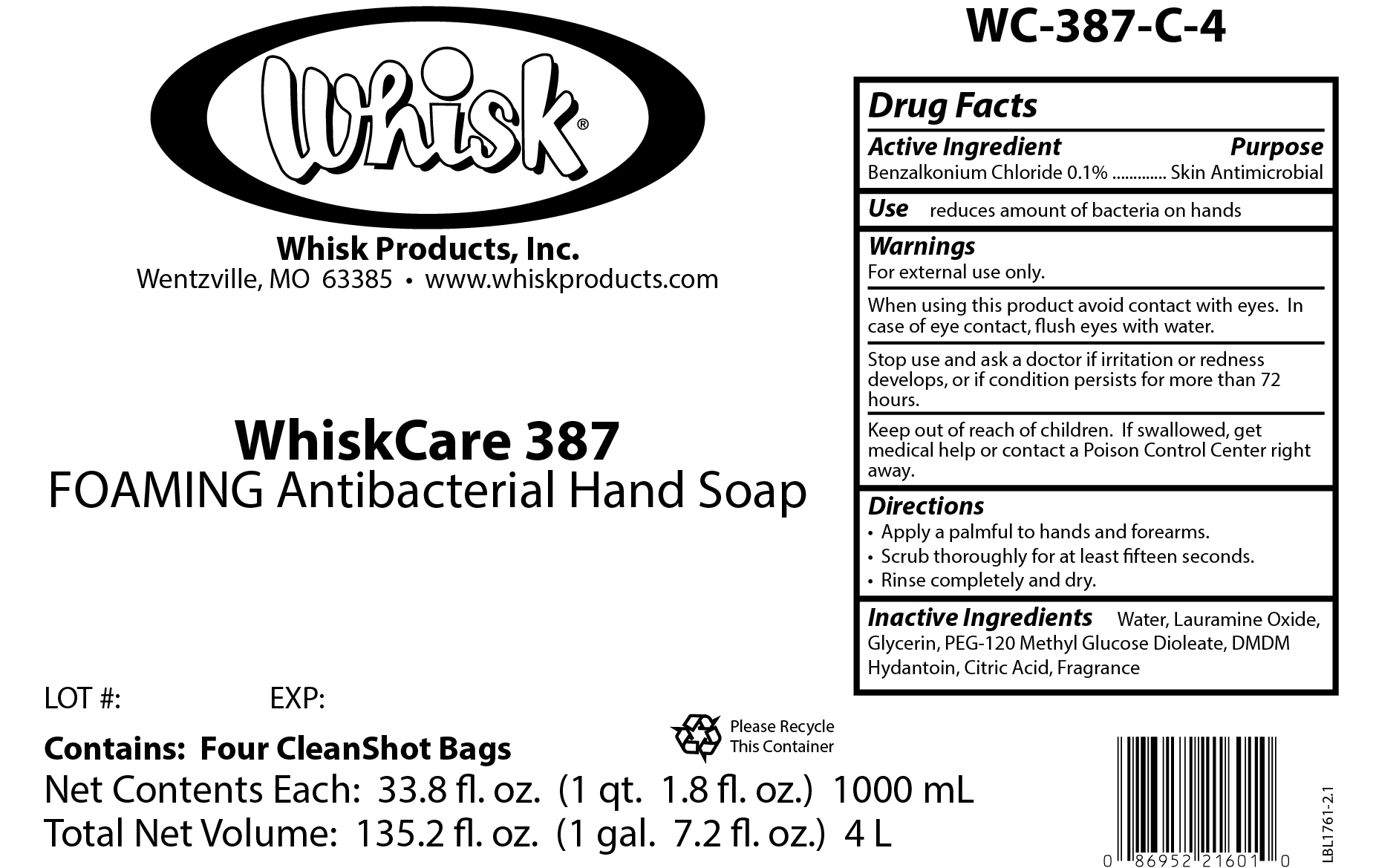 DRUG LABEL: WhiskCare 387
NDC: 65585-513 | Form: SOAP
Manufacturer: Whisk Products, Inc.
Category: otc | Type: HUMAN OTC DRUG LABEL
Date: 20250522

ACTIVE INGREDIENTS: BENZALKONIUM CHLORIDE 1 mg/1 mL
INACTIVE INGREDIENTS: WATER; PEG-120 METHYL GLUCOSE DIOLEATE; LAURAMINE OXIDE; DMDM HYDANTOIN; CITRIC ACID MONOHYDRATE; GLYCERIN

WhiskCare 387

Active Ingredient

Benzalkonium Chloride 0.1%

Purpose

Skin Antimicrobial

Use

reduces amount of bacteria on hands

Warnings

For external use only.

When using this product avoid contact with eyes. In case of eye contact, flush eyes with water.

Stop use and ask a doctor if irritation or redness develops, or if condition persists for more than 72 hours.

Keep out of reach of children. If swallowed, get medical help or contact a Poison Control Center right away.

Directions

- Apply a palmful to hands and forearms.
- Scrub thoroughly for at least fifteen seconds.
- Rinse completely and dry.

Inactive Ingredients

Water, Lauramine Oxide, Glycerin, PEG-120 Methyl Glucose Dioleate, DMDM Hydantoin, Citric Acid, Fragrance